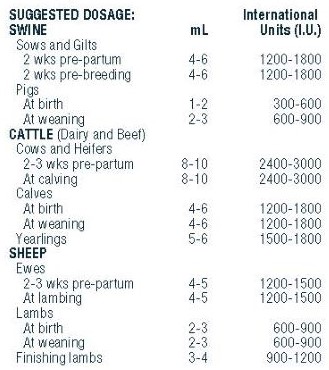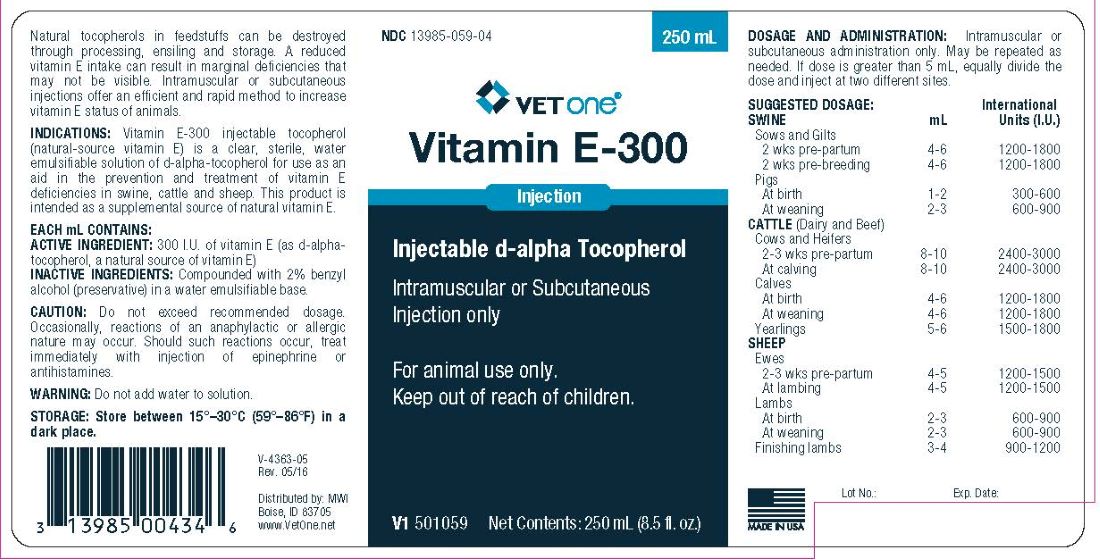 DRUG LABEL: Vitamin E-300
NDC: 13985-059 | Form: INJECTION
Manufacturer: MWI/VetOne
Category: animal | Type: OTC ANIMAL DRUG LABEL
Date: 20231206

ACTIVE INGREDIENTS: ALPHA-TOCOPHEROL 300 mg/300 mL

Vitamin E-300

DESCRIPTION

Vitamin E-300

Injectable d-alpha Tocopherol
Intramuscular or Subcutaneous Injection only

For animal use only.
Keep out of reach of children

Dosage and Administration: Intramuscular or subcutaneous administration only. May be repeated as needed. If dose is greater than 5 mL, equally divide the dose and inject at two different sites.

PURPOSE

Natural tocopherols in feedstuffs can be destroyed through process, ensiling and storage. A reduced vitamin E intake can result in marginal deficiencies that may not be visible. Intramuscular or subcutaneous injections offer an efficient and rapid method to increase vitamin E status of animals.

INDICATIONS

Vitamin E-300 Injectable Tocopherol (natural-source vitamin E) is a clear, sterile, water emulsifiable solution of d-alpha-tocopherol for use as an aid in the prevention and treatment of vitamin E deficiencies in swine, cattle and sheep. This product is intended as a supplemental source of natural vitamin E.

Each mL contains:

Active Ingredient: 300 I.U. of vitamin E (as d-alpha-tocopherol, a natural source of vitamin E);

Inactive Ingredients: Compounded with 2% benzyl alcohol (preservative) in a water emulsifiable base.

CAUTION

Do not exceed recommended dosage. Occasionally, reactions of an anaphylactic or allergic nature may occur. Should such reactions occur, treat immediately with injection of epinephrine or antihistamines.

WARNINGS

Do not add water to solution.

STORAGE AND HANDLING

Store between 15°–30°C (59°–86°F) in a dark place.